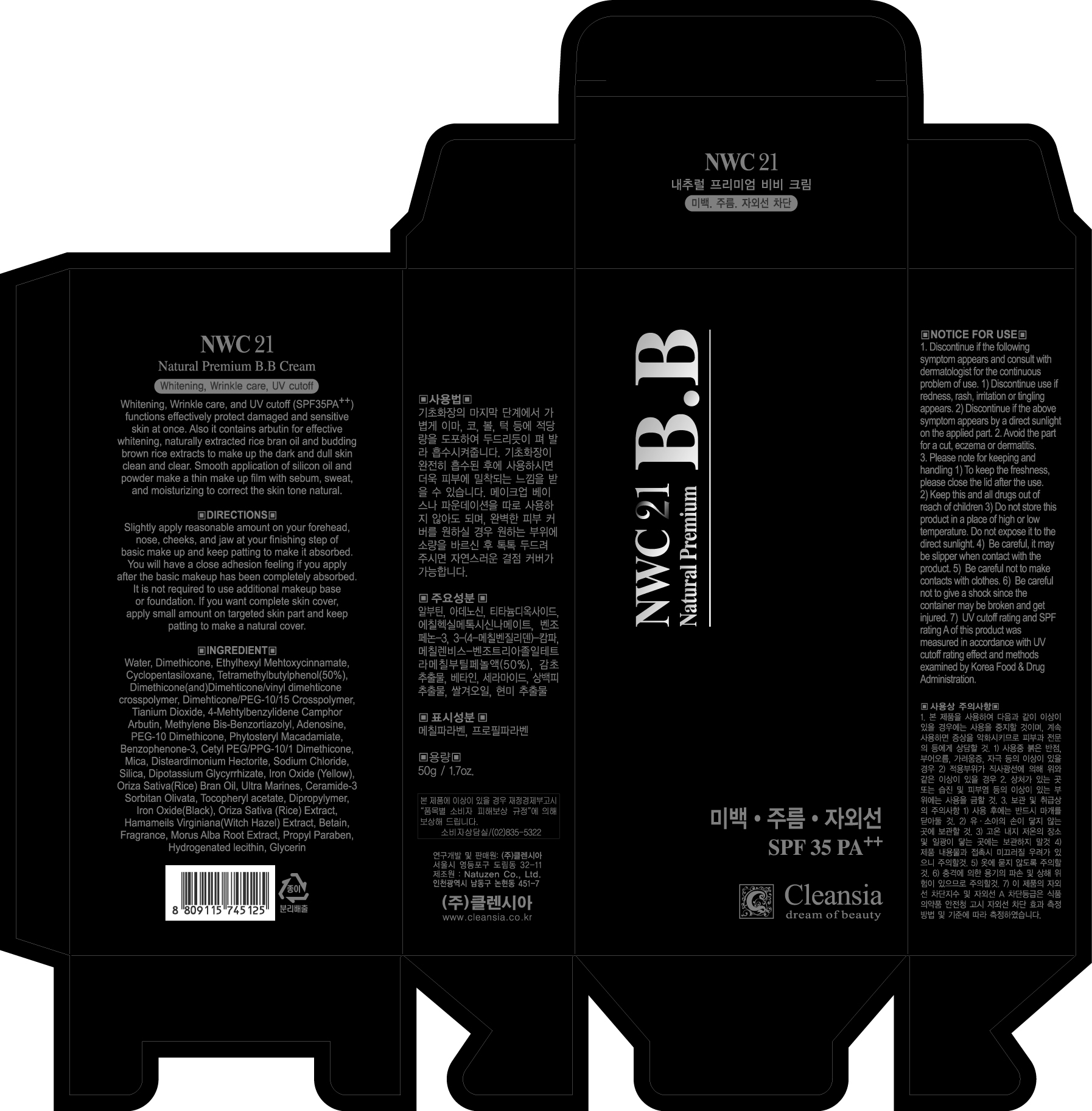 DRUG LABEL: NWC 21 NATURAL PREMIUM BB CREAM
NDC: 45167-451 | Form: CREAM
Manufacturer: Cleansia Co Ltd
Category: otc | Type: HUMAN OTC DRUG LABEL
Date: 20100121

ACTIVE INGREDIENTS: OCTINOXATE 3.75 g/50 g; TITANIUM DIOXIDE 1.1 g/50 g; ENZACAMENE 1.0 g/50 g

Active Ingredients:
Ethylhexyl Methoxycinnamate, Titanium Dioxide, 4-Methylbenzylidene Camphor, Methylene Bis-Benzotriazolyl Tetramethylbutylphenol, Arbutin, Benzophenone-3, Adenosine

Inactive Ingredients:
Water, Dimethicone, Cyclopentasiloxane, Dimethicone/Vinyl Dimethicone Crosspolymer, Dipropylene Glycol, Dimethicone/PEG-10/15 Crosspolymer, Glycerin, Propylene glycol, Cetyl PEG/PPG-10/1 Dimethicone, Disteardimonium Hectorite, Phytosteryl Macadamiate, PEG-10 Dimethicone, Silica dimethyl silylate, Betaine, Methylparaben, Oryza Sativa (Rice) bran Oil, Silica, Mica, Dipotassium Glycyrrhizate, Sodium Citrate, Oryza sativa (Rice) Bran extract, Propylparaben, Sodium Chloride, Iron Oxides, Ultramarines, Sorbitan Olivate, Tocopheryl Acetate, Xanthan Gum, Fragrance, Hydrogenated lecithin, Morus Alba Root Extract, ceramide-3

Directions:
Slightly apply reasonable amount on your forehead, nose, cheeks and jaw at your finishing step of basic make up and keep patting to make it absorbed. You will have a close adhesion feeling if you apply after the basic makeup has been completely absorbed. It is not required to use additional make up base or foundation. If you want complete skin cover, apply small amount on targeted skin part and keep patting to make a natural cover.

Notice for Use:
1. Discontinue if the following symptom appears and consult with dermatologist for the continuous problem of use
a) Discontinue use if redness, rash, irritation or tingling appears
b) Discontinue if the above symptom appears by a direct sunlight on the applied part
2. Avoid the part for a cut, eczema or dermatitis

KEEP OUT OF REACH OF CHILDREN

Keep this and all drugs out of reach of children

PRECAUTIONS

Caution:
- Be careful it may be slippery when contact with the product
- Be careful not to make contact with clothes
- Be careful not to give a shock since the container may be broken and get injured

Storage and Handling:
- To keep the freshness, please close the lid after the use
- Do not store this product in a place of high or low temperature
- Do not expose it to the direct sunlight